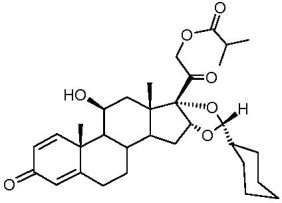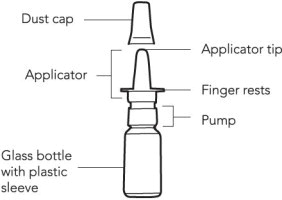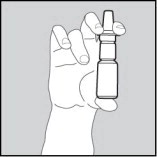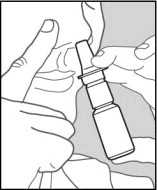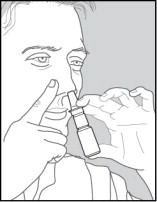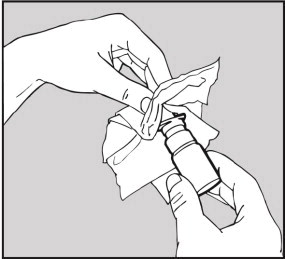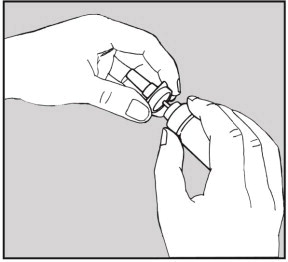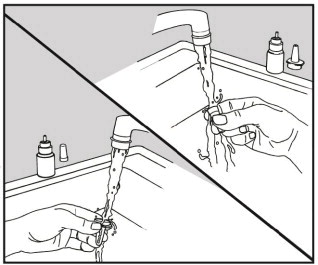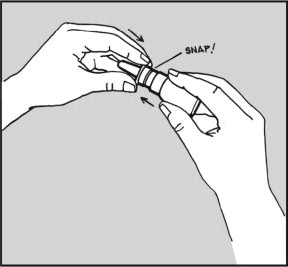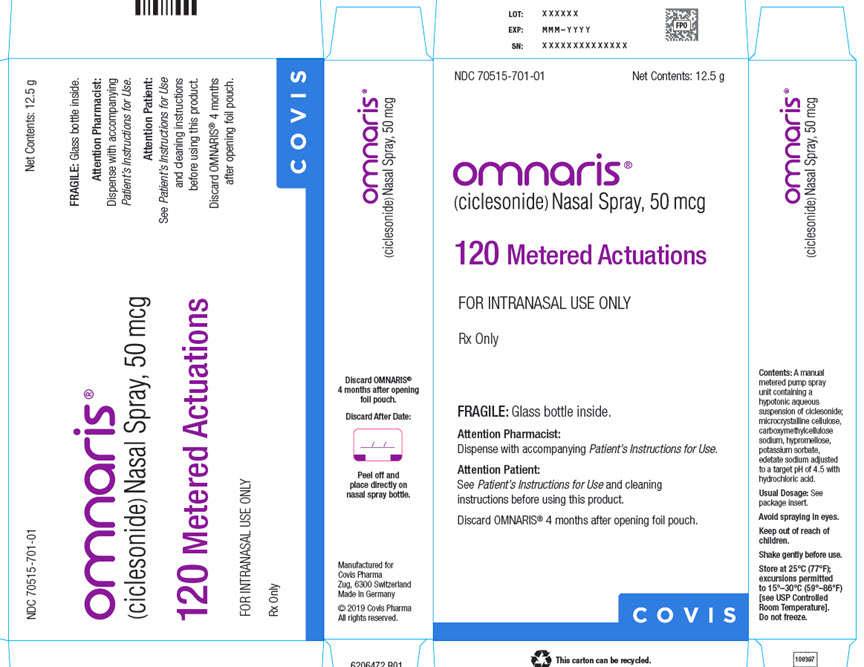 DRUG LABEL: Omnaris
NDC: 70515-701 | Form: SPRAY
Manufacturer: Covis Pharma US, Inc
Category: prescription | Type: HUMAN PRESCRIPTION DRUG LABEL
Date: 20221108

ACTIVE INGREDIENTS: CICLESONIDE 50 ug/1 1
INACTIVE INGREDIENTS: MICROCRYSTALLINE CELLULOSE; CARBOXYMETHYLCELLULOSE SODIUM, UNSPECIFIED FORM; HYPROMELLOSE, UNSPECIFIED; POTASSIUM SORBATE; EDETATE DISODIUM; HYDROCHLORIC ACID; WATER

HIGHLIGHTS OF PRESCRIBING INFORMATION

These highlights do not include all the information needed to use OMNARIS® safely and effectively. See full prescribing information for OMNARIS.
OMNARIS® (ciclesonide) nasal spray
Initial U.S. Approval: 2006

1 INDICATIONS AND USAGE

OMNARIS Nasal Spray is a corticosteroid indicated for treatment of nasal symptoms associated with seasonal allergic rhinitis in adults and children 6 years of age and older and perennial allergic rhinitis in adults and adolescents 12 years of age and older. (1.1, 1.2)

2 DOSAGE AND ADMINISTRATION

For Intranasal Use Only

- 2 sprays per nostril once daily. (200 mcg) (2.1, 2.2)
- Priming Information: Gently shake and prime OMNARIS Nasal Spray before using for the first time or when not used for four consecutive days. (2)

3 DOSAGE FORMS AND STRENGTHS

Nasal Spray: 50 mcg of ciclesonide in each 70-microliter spray. (3)

4 CONTRAINDICATIONS

Patients with a known hypersensitivity to ciclesonide or any of the ingredients of OMNARIS Nasal Spray. (4)

5 WARNINGS AND PRECAUTIONS

- Epistaxis, Candida albicans infection, nasal septal perforation, impaired wound healing. Monitor patients periodically for signs of adverse effects on the nasal mucosa. Avoid spraying OMNARIS directly onto the nasal septum. Avoid use in patients with recent nasal ulcers, nasal surgery, or nasal trauma. (5.1)
- Development of glaucoma or cataracts. Monitor patients closely with a change in vision or with a history of increased intraocular pressure, glaucoma, and/or cataracts. (5.2)
- Potential worsening of existing tuberculosis; fungal, bacterial, viral, or parasitic infections, or ocular herpes simplex. More serious or even fatal course of chickenpox or measles in susceptible patients. Use caution in patients with the above because of the potential for worsening of these infections. (5.3)
- Hypercorticism and adrenal suppression with very high dosages or at the regular dosage in susceptible individuals. If such changes occur, discontinue OMNARIS Nasal Spray slowly. (5.4)
- Potential reduction in growth velocity in children. Monitor growth routinely in pediatric patients receiving OMNARIS Nasal Spray. (5.5, 8.4)

6 ADVERSE REACTIONS

The most common adverse reactions (>2% incidence) included headache, epistaxis, nasopharyngitis, ear pain, and pharyngolaryngeal pain. (6)

To report SUSPECTED ADVERSE REACTIONS, contact Covis Pharma at 1-866-488-4423 or FDA at 1-800-FDA-1088 or www.fda.gov/medwatch.

FULL PRESCRIBING INFORMATION

1 INDICATIONS AND USAGE

1.1 Treatment of Seasonal Allergic Rhinitis

OMNARIS Nasal Spray is indicated for the treatment of nasal symptoms associated with seasonal allergic rhinitis in adults and children 6 years of age and older.

1.2 Treatment of Perennial Allergic Rhinitis

OMNARIS Nasal Spray is indicated for the treatment of nasal symptoms associated with perennial allergic rhinitis in adults and adolescents 12 years of age and older.

2 DOSAGE AND ADMINISTRATION

Administer OMNARIS Nasal Spray by the intranasal route only. Prior to initial use, OMNARIS Nasal Spray must be gently shaken and then the pump must be primed by actuating eight times. If the product is not used for four consecutive days, it should be gently shaken and reprimed with one spray or until a fine mist appears. Illustrated patient’s instructions for proper use accompany each package of OMNARIS Nasal Spray.

2.1 Seasonal Allergic Rhinitis

Adults and Children (6 Years of Age and Older): The recommended dose of OMNARIS Nasal Spray is 2 sprays per nostril once daily (200 mcg). The maximum total daily dosage should not exceed 2 sprays in each nostril (200 mcg/day).

2.2 Perennial Allergic Rhinitis

Adults and Adolescents (12 Years of Age and Older): The recommended dose of OMNARIS Nasal Spray is 2 sprays per nostril once daily (200 mcg). The maximum total daily dosage should not exceed 2 sprays in each nostril (200 mcg/day).

3 DOSAGE FORMS AND STRENGTHS

OMNARIS Nasal Spray is a metered-dose, manual-pump spray formulation containing a hypotonic aqueous suspension of ciclesonide. Once primed, each actuation of the pump delivers 50 mcg ciclesonide in a volume of 70 microliters from the nasal actuator.

4 CONTRAINDICATIONS

OMNARIS Nasal Spray is contraindicated in patients with a known hypersensitivity to ciclesonide or any of the ingredients of OMNARIS Nasal Spray [see Warnings and Precautions (5.3)].

5 WARNINGS AND PRECAUTIONS

5.1 Local Nasal Effects

Epistaxis: In clinical studies of 2 to 52 weeks’ duration, epistaxis was observed more frequently in patients treated with OMNARIS Nasal Spray than those who received placebo [see Adverse Reactions (6)].

Candida Infection: In clinical studies with OMNARIS Nasal Spray, the development of localized infections of the nose and pharynx with Candida albicans has occurred. When such an infection develops, it may require treatment with appropriate local therapy and discontinuation of OMNARIS Nasal Spray. Therefore, patients using OMNARIS Nasal Spray over several months or longer should be examined periodically for evidence of Candida infection or other signs of adverse effects on the nasal mucosa.

Nasal Septal Perforation: Instances of nasal septal perforation have been reported in patients following the intranasal application of corticosteroids. No cases of nasal septal perforation were identified in clinical studies with OMNARIS Nasal Spray. Avoid spraying OMNARIS Nasal Spray directly onto the nasal septum.

Impaired Wound Healing: Because of the inhibitory effect of corticosteroids on wound healing, patients who have experienced recent nasal septal ulcers, nasal surgery, or nasal trauma should not use a nasal corticosteroid until healing has occurred.

5.2 Glaucoma and Cataracts

Nasal and inhaled corticosteroids may result in the development of glaucoma and/or cataracts. Therefore, close monitoring is warranted in patients with a change in vision or with a history of increased intraocular pressure, glaucoma, and/or cataracts.

The risk of glaucoma was evaluated by assessments of intraocular pressure in 3 studies including 943 patients. Of these, 390 adolescents or adults were treated for up to 52 weeks and 186 children ages 2 to 11 received treatment with OMNARIS Nasal Spray 200 mcg daily for up to 12 weeks. In these studies, no significant differences in intraocular pressure changes were observed between OMNARIS Nasal Spray 200 mcg and placebo-treated patients. Additionally, no significant differences between OMNARIS Nasal Spray 200 mcg and placebo-treated patients were noted during the 52-week study of adults and adolescent patients in whom thorough ophthalmologic assessments were performed, including evaluation of cataract formation using slit lamp examinations.

5.3 Immunosuppression

Patients who are using drugs that suppress the immune system are more susceptible to infections than healthy individuals. Chickenpox and measles, for example, can have a more serious or even fatal course in susceptible children or adults using corticosteroids. In children or adults who have not had these diseases or been properly immunized, particular care should be taken to avoid exposure. How the dose, route, and duration of corticosteroid administration affect the risk of developing a disseminated infection is not known. The contribution of the underlying disease and/or prior corticosteroid treatment to the risk is also not known. If a patient is exposed to chickenpox, prophylaxis with varicella zoster immune globulin (VZIG) may be indicated. If a patient is exposed to measles, prophylaxis with pooled intramuscular immunoglobulin (IG) may be indicated (see the respective package inserts for complete VZIG and IG prescribing information.) If chickenpox develops, treatment with antiviral agents may be considered.

Corticosteroids should be used with caution, if at all, in patients with active or quiescent tuberculosis infections of the respiratory tract; or in patients with untreated local or systemic fungal or bacterial infections; systemic viral or parasitic infections; or ocular herpes simplex because of the potential for worsening of these infections.

5.4 Hypothalamic-Pituitary-Adrenal Axis Effect

Hypercorticism and Adrenal Suppression: When intranasal corticosteroids are used at higher than recommended dosages or in susceptible individuals at recommended dosages, systemic corticosteroid effects such as hypercorticism and adrenal suppression may appear. If such changes occur, the dosage of OMNARIS Nasal Spray should be discontinued slowly, consistent with accepted procedures for discontinuing oral steroid therapy.

The replacement of a systemic corticosteroid with a topical corticosteroid can be accompanied by signs of adrenal insufficiency. In addition, some patients may experience symptoms of corticosteroid withdrawal, e.g., joint and/or muscular pain, lassitude, and depression. Patients previously treated for prolonged periods with systemic corticosteroids and transferred to topical corticosteroids should be carefully monitored for acute adrenal insufficiency in response to stress. In those patients who have asthma or other clinical conditions requiring long-term systemic corticosteroid treatment, rapid decreases in systemic corticosteroid dosages may cause a severe exacerbation of their symptoms.

5.5 Effect on Growth

Corticosteroids may cause a reduction in growth velocity when administered to pediatric patients. Monitor the growth routinely (e.g., via stadiometry) in pediatric patients receiving OMNARIS Nasal Spray.

6 ADVERSE REACTIONS

Systemic and local corticosteroid use may result in the following:

- Epistaxis, nasal septal perforations, Candida albicans infection, impaired wound healing [see Warnings and Precautions (5.1)]
- Cataracts and glaucoma [see Warnings and Precautions (5.2)]
- Immunosuppression [see Warnings and Precautions (5.3)]
- Hypothalamic-pituitary-adrenal (HPA) axis effects, including growth reduction [see Warnings and Precautions (5.4, 5.5), Use in Specific Populations (8.4)]

6.1 Clinical Trials Experience

Because clinical trials are conducted under widely varying conditions, adverse reaction rates observed in clinical trials of a drug cannot be directly compared to rates in the clinical trials of another drug and may not reflect the rates observed in practice.

The safety data described below for adults and adolescents 12 years of age and older are based on 3 clinical trials of 2 to 6 weeks duration and one 52-week trial. In the 3 trials of 2 to 6 weeks duration, 1524 patients (495 males and 1029 females, ages 12 to 86 years old) with seasonal or perennial allergic rhinitis were treated with OMNARIS Nasal Spray 200, 100, 50, or 25 mcg or placebo once daily. The racial distribution in these three trials included 1374 Caucasians, 69 Blacks, 31 Asians, and 50 patients classified as Other. The 52-week trial was conducted in 663 patients (227 males and 436 females, ages 12 to 73 years old) treated with OMNARIS Nasal Spray 200 mcg or placebo once daily. The racial distribution in this trial included 538 Caucasians, 69 Blacks, 16 Asians, and 40 patients classified as Other. The data from pediatric patients are based upon 4 clinical trials in which 1541 children (871 males and 670 females, ages 2 to 11 years old) with seasonal or perennial allergic rhinitis were treated with OMNARIS Nasal Spray 200, 100, or 25 mcg or placebo once daily for 2 to 12 weeks. The racial distribution in these four trials included 1136 Caucasians, 273 Blacks, 20 Asians, and 112 patients classified as Other.

Adults and Adolescents 12 Years of Age and Older in Short-Term (2-6 weeks) Trials: In three short-term trials conducted in the US and Canada, 546 patients were treated with OMNARIS Nasal Spray 200 mcg daily. Adverse reactions did not differ appreciably based on age, gender, or race. Approximately 2% of patients treated with OMNARIS Nasal Spray 200 mcg in clinical trials discontinued because of adverse reactions; this rate was similar for patients treated with placebo. The table below displays reactions that occurred with an incidence of 2% or greater and more frequently with OMNARIS Nasal Spray 200 mcg than with placebo in clinical trials of 2 to 6 weeks in duration.

Table 1 Adverse Events from Controlled Clinical Trials 2 to 6 Weeks in Duration in Patients 12 Years of Age and Older with Seasonal or Perennial Allergic Rhinitis
Adverse Event | OMNARIS Nasal Spray 200 mcg Once Daily (N = 546) % | Placebo (N = 544) %
Headache | 6.0 | 4.6
Epistaxis | 4.9 | 2.9
Nasopharyngitis | 3.7 | 3.3
Ear Pain | 2.2 | 0.6

Pediatric Patients Aged 6 to 11 Years in Short-Term (2-12 weeks) Trials: In two short-term trials, conducted in the US and Canada, 913 patients were treated with OMNARIS Nasal Spray 200 mcg, 100 mcg or 25 mcg daily. Adverse events did not differ appreciably based on age, gender, or race. In clinical trials, 1.6% and 2.7% of patients treated with OMNARIS Nasal Spray 200 mcg or 100 mcg, respectively, discontinued because of adverse reactions; these rates were lower than the rate in patients treated with placebo (2.8%). Table 2 displays adverse events that occurred with an incidence of 3% or greater and more frequently with OMNARIS Nasal Spray 200 mcg than with placebo.

Table 2 Adverse Events from Controlled Clinical Trials 2 to 12 Weeks in Duration in Patients 6 to 11 Years of Age and Older with Seasonal or Perennial Allergic Rhinitis
Adverse Event | OMNARIS Nasal Spray 200 mcg Once Daily (N = 380) % | Placebo (N = 369) %
Headache | 6.6 | 5.7
Nasopharyngitis | 6.6 | 5.4
Pharyngolaryngeal pain | 3.4 | 3.3

Pediatric Patients Aged 2 to 5 Years in Short-Term (6-12 weeks) Trials: In two short-term trials conducted in the US, 183 patients were treated with OMNARIS Nasal Spray 200 mcg, 100 mcg or 25 mcg daily. The distribution of adverse events was similar to that seen in the 6 to 11 year old children.

Long-Term (52-Week) Safety Trial: In a 52-week double-blind, placebo-controlled safety trial that included 663 adults and adolescent patients (441 treated with ciclesonide: 227 males and 436 females) with perennial allergic rhinitis, the adverse reaction profile over the treatment period was similar to the adverse event profile in trials of shorter duration. Adverse reactions, irrespective of drug relationship, that occurred with an incidence of 3% or greater and more frequently with OMNARIS Nasal Spray 200 mcg than with placebo were epistaxis, pharyngolaryngeal pain, sinusitis, headache, nasal discomfort, cough, bronchitis, influenza, back pain, and urinary tract infection. No patient experienced a nasal septal perforation or nasal ulcer during this long-term trial of OMNARIS Nasal Spray.

6.2 Post-Marketing Experience

The following adverse reactions have been reported in association with post-marketing use of OMNARIS Nasal Spray and are not listed above: nasal congestion, nasal ulcer and dizziness. Because these reactions are reported voluntarily from a population of uncertain size, it is not always possible to reliably estimate their frequency or to establish a causal relationship to drug exposure.

7 DRUG INTERACTIONS

In vitro studies and clinical pharmacology studies suggested that des-ciclesonide has no potential for metabolic drug interactions or protein binding-based drug interactions [see Clinical Pharmacology (12.3)].

In a drug interaction study, co-administration of orally inhaled ciclesonide and oral ketoconazole, a potent inhibitor of cytochrome P450 3A4, increased the exposure (AUC) of des-ciclesonide by approximately 3.6-fold at steady state, while levels of ciclesonide remained unchanged. Erythromycin, a moderate inhibitor of cytochrome P450 3A4, had no effect on the pharmacokinetics of either des-ciclesonide or erythromycin following oral inhalation of ciclesonide [see Clinical Pharmacology (12.3)].

8 USE IN SPECIFIC POPULATIONS

8.1 Pregnancy

Risk Summary

There are no data on ONMARIS nasal spray use in pregnant women to assess a drug associated risk of major birth defects, miscarriage, or adverse maternal or fetal outcomes. There is low systemic exposure following OMNARIS nasal spray administration at the recommended dose [see Clinical Pharmacology (12.3)].

In animal reproduction studies, ciclesonide, administered by the oral route to pregnant rats, during the period of organogenesis, did not cause any evidence of fetal harm at doses up 45 times the maximum recommended human daily intranasal dose (MRHDID) of 200 mcg/day. Teratogenicity, characteristic of corticosteroids, decreased body weight and/or skeletal variations were observed in rabbit fetuses following administration of ciclesonide to pregnant rabbits by the subcutaneous route during the period of organogenesis at doses 0.5 times the MRHDID and higher on a mcg/m^2 basis (see Data). No evidence of fetal harm was observed in rabbits at doses 0.1 times the MRHDID.

All pregnancies have a background risk of birth defect, loss, or other adverse outcomes. The estimated background risk of major birth defects and miscarriage for the indicated population is unknown. In the United States general population, the estimated background risk of major birth defects and miscarriage in clinically recognized pregnancies is 2% to 4% and 15% to 20%, respectively.

Data

Animal Data

In an embryo-fetal development study in pregnant rats dosed by the oral route during the period of organogenesis from gestation days 6 to 15, ciclesonide did not cause any evidence of fetal harm at doses up to 45 times the MRHDID in adults (on a mcg/m^2 basis with maternal oral dose up to 900 mcg/kg/day). Maternal toxicity, as evidenced by decreased body weight gain, was observed at 45 times the MRHDID in adults (on a mcg/m^2 basis at a maternal dose of 900 mcg/kg/day); however, no adverse effects were observed at doses 15 times the MRHDID and lower (on a mcg/m^2 basis with maternal oral doses of 300 mcg/kg/day and lower).

In two embryo-fetal development studies in pregnant rabbits dosed by the subcutaneous route during the period of organogenesis from gestation days 6 to 18, ciclesonide caused acampsia (flexures of legs) in fetuses at doses 0.5 times the MRHDID and higher (on a mcg/m^2 basis with maternal oral doses of 5 mcg/kg/day and higher), decreased body weight, cleft palate, enlarged fontanelle, parchment-like skin, and incomplete ossification of bones in fetuses at doses 2 times the MRHDID (on a mcg/m^2 basis with a maternal subcutaneous dose of 25 µg/kg/day) and embryo-fetal death at doses 10 times the MRHDID and higher (on a mcg/m^2 basis at maternal subcutaneous doses of 100 mcg/kg/day and higher). No evidence of fetal harm was observed at a dose 0.1 times the MRHDID in adults (on a mcg/m^2 basis at a maternal subcutaneous dose of 1 mcg/kg/day). Maternal toxicity was observed at doses 10 times the MRHDID in adults (on a mcg/m^2 basis with maternal subcutaneous doses of 100 mcg/kg/day and lower); however, no evidence of toxicity was observed at doses 2 times the MRHDID and lower (on a mcg/m^2 basis with maternal subcutaneous doses of 25 mcg/kg/day and lower).

In a prenatal and postnatal development study in pregnant rats dosed by the oral route from gestation day 6 to lactation day 20, ciclesonide produced no adverse developmental effects on offspring at doses up to approximately 45 times the MRHDID (on mcg/m^2 bases at maternal oral doses up to 900 mcg/kg/day).

8.2 Lactation

Risk Summary

There are no data on the presence of ciclesonide in human milk, the effects on the breastfed child, or on milk production. It is not known whether nasal spray administration of ciclesonide at the recommended dose could result in sufficient systemic absorption to produce detectable quantities in human milk [see Clinical Pharmacology (12.3)]. The developmental and health benefits of breastfeeding should be considered along with the mother’s clinical need for OMNARIS Nasal Spray, and any potential adverse effects on the breastfed child from OMNARIS Nasal Spray, or from the underlying maternal condition.

Clinical Considerations

The pharmacokinetics of intranasally administered ciclesonide have not been assessed in patient subpopulations because the resulting blood levels of ciclesonide and des-ciclesonide are insufficient for pharmacokinetic calculations [see Clinical Pharmacology (12.3)].

The molecular weight of the prodrug ciclesonide (approximately 541 g/mol) is small enough to be excreted into breast milk; however, its high plasma protein binding affinity and very short half-life suggest that minimal amounts will be present within the milk. Conversely, the half-life of the active metabolite des-ciclesonide (approximately 471 g/mol) suggests that exposure to the nursing infant will be greater than that of the prodrug ciclesonide. Although ciclesonide and des-ciclesonide have negligible oral bioavailability (both less than 1% for each) due to low gastrointestinal absorption and high first-pass metabolism, the relative anti‑inflammatory activity of des-ciclesonide is 12-times greater than that of dexamethasone. The effects of this exposure on a nursing infant are unknown, however, like all corticosteroids, suppression of the HPA function is a potential complication.

Data

Human Data

At recommended doses, the intranasal administration of ciclesonide results in negligible serum concentrations of ciclesonide. However, the known active metabolite (des‑ciclesonide) is detected in the serum of some patients after nasal inhalation of ciclesonide. The bioanalytical assay used has a lower limit of quantification of 25 pg/mL and 10 pg/mL, for ciclesonide and des-ciclesonide, respectively.

In healthy adults treated for 2 weeks with 50 to 800 mcg of ciclesonide nasal spray daily (n = 6 in each treatment group), the peak serum concentrations of des-ciclesonide in all subjects were found to be below 30 pg/mL. Of those treated with 800 mcg and 400 mcg daily, 100% and 67% had detectable levels of des-ciclesonide, respectively. With daily doses of ≤ 200 mcg, detectable serum levels of des-ciclesonide were not observed. The low systemic exposure following ciclesonide nasal spray administration was confirmed in a crossover study in 29 healthy adults. The median maximum observed concentration was less than 10 pg/mL and 602 pg/mL following a single dose of ciclesonide nasal spray (300 mcg) and orally inhaled ciclesonide (320 mcg), respectively.

Animal Data

A study with ^14C-ciclesonide showed milk exposure of rat pups to 0.006% of the dose secreted in milk.

8.4 Pediatric Use

The safety and effectiveness for seasonal and perennial allergic rhinitis in children 12 years of age and older have been established. The efficacy of OMNARIS Nasal Spray in patients 6 to 11 years of age for treatment of the symptoms of seasonal allergic rhinitis was demonstrated in one study in patients 6 to 11 years of age with seasonal allergic rhinitis. The efficacy of OMNARIS Nasal Spray for the treatment of the symptoms of seasonal allergic rhinitis in patients 5 years of age and younger has not been established. The efficacy of OMNARIS Nasal Spray for the treatment of the symptoms of perennial allergic rhinitis in patients 11 years of age and younger has not been established [see Clinical Studies (14.1)]. The safety of OMNARIS Nasal Spray in children 2 to 11 years of age was evaluated in 4 controlled clinical studies of 2 to 12 weeks duration [see Clinical Pharmacology (12.2), Clinical Studies (14.1), and Adverse Reactions (6)].

Controlled clinical studies have shown that intranasal corticosteroids may cause a reduction in growth velocity in pediatric patients. This effect has been observed in the absence of laboratory evidence of hypothalamic-pituitary-adrenal (HPA)-axis suppression, suggesting that growth velocity is a more sensitive indicator of systemic corticosteroid exposure in pediatric patients than some commonly used tests of HPA-axis function. The long-term effects of this reduction in growth velocity associated with intranasal corticosteroids, including the impact on final adult height, are unknown. The potential for “catch-up” growth following discontinuation of treatment with intranasal corticosteroids has not been adequately studied. The growth of pediatric patients receiving intranasal corticosteroids, including OMNARIS Nasal Spray, should be monitored routinely (e.g., via stadiometry). A 52-week, multicenter, double-blind, randomized, placebo-controlled parallel-group study was conducted to assess the effect of orally inhaled ciclesonide on growth rate in 609 pediatric patients with mild persistent asthma, aged 5 to 8.5 years. Treatment groups included orally inhaled ciclesonide 40 mcg or 160 mcg or placebo given once daily. Growth was measured by stadiometer height during the baseline, treatment and follow-up periods. The primary comparison was the difference in growth rates between ciclesonide 40 and 160 mcg and placebo groups. Conclusions cannot be drawn from this study because compliance could not be assured. Ciclesonide blood levels were also not measured during the one-year treatment period. There was no difference in efficacy measures between the placebo and the orally inhaled ciclesonide groups.

The potential growth effects of prolonged treatment should be weighed against clinical benefits obtained and the availability of safe and effective noncorticosteroid treatment alternatives. To minimize the systemic effects of intranasal corticosteroids, each patient should be titrated to the lowest dose that effectively controls his/her symptoms.

8.5 Geriatric Use

Clinical studies of OMNARIS Nasal Spray did not include sufficient numbers of subjects aged 65 and over to determine whether they respond differently from younger subjects. Other reported clinical experience has not identified differences in responses between the elderly and younger patients. In general, dose selection for an elderly patient should be cautious, usually starting at the low end of the dosing range, reflecting the greater frequency of decreased hepatic, renal, or cardiac function, and of concomitant disease or other drug therapy.

10 OVERDOSAGE

Chronic overdosage may result in signs or symptoms of hypercorticism [see Warnings and Precautions (5.4)].

There are no data available on the effects of acute or chronic overdosage with OMNARIS Nasal Spray.

11 DESCRIPTION

The active component of OMNARIS Nasal Spray is ciclesonide, a non-halogenated glucocorticoid having the chemical name pregna -1,4-diene-3,20-dione, 16,17-[[R-cyclohexylmethylene]bis(oxy)]-11-hydroxy-21-(2-methyl-1-oxopropoxy)-,(11β,16α)-. Ciclesonide is delivered as the R-epimer. The empirical formula is C32H44O7 and its molecular weight is 540.7. Its structural formula is as follows:

Ciclesonide is a white to yellow-white powder, practically insoluble in water and freely soluble in ethanol and acetone. OMNARIS Nasal Spray is a metered-dose, manual-pump spray formulation containing a hypotonic aqueous suspension of ciclesonide. OMNARIS Nasal Spray also contains microcrystalline cellulose, carboxymethylcellulose sodium, hypromellose, potassium sorbate and edetate sodium; and hydrochloric acid to adjust the pH to 4.5.

12 CLINICAL PHARMACOLOGY

12.1 Mechanism of Action

Ciclesonide is a pro-drug that is enzymatically hydrolyzed to a pharmacologically active metabolite, C21-desisobutyryl-ciclesonide (des-ciclesonide or RM1) following intranasal application. Des-ciclesonide has anti-inflammatory activity with affinity for the glucocorticoid receptor that is 120-times higher than the parent compound.

The precise mechanism through which ciclesonide affects allergic rhinitis symptoms is not known. Corticosteroids have been shown to have a wide range of effects on multiple cell types (e.g., mast cells, eosinophils, neutrophils, macrophages, and lymphocytes) and mediators (e.g., histamine, eicosanoids, leukotrienes, and cytokines) involved in allergic inflammation.

12.2 Pharmacodynamics

Adrenal Function: In a 6-week trial in adolescents and adults 12-73 years of age with perennial allergic rhinitis, a daily dose of 200 mcg of OMNARIS Nasal Spray was compared to placebo nasal spray. Dexamethasone 6 mg was used as an active control during the last 4 days of the treatment period. Adrenal function was assessed by measurement of 24-hour serum cortisol levels before and after 6 consecutive weeks of treatment. The difference from placebo for the change from baseline in serum cortisol AUC(0-24) was 10.4 mcg•hour/dL (95% CI: -4.7, 25.5) for 200 mcg of OMNARIS Nasal Spray. The effects observed with the active control (dexamethasone, n=18) validate the sensitivity of the study to assess the effect of ciclesonide on the HPA axis.

In a 12-week study in children 6 to 11 years of age with perennial allergic rhinitis, daily doses of 200 mcg, 100 mcg, and 25 mcg of OMNARIS Nasal Spray were compared to placebo nasal spray. Adrenal function was assessed by measurement of 24-hour urinary-free cortisol (in 32 to 44 patients per group) and morning plasma cortisol levels (in 45 to 61 patients per group) before and after 12 consecutive weeks of treatment. The ciclesonide-treated groups had a numerically greater decline in 24-hour urinary-free cortisol compared to the placebo-treated group. The differences (and 95% confidence intervals) from placebo in the mean change from baseline to 12 weeks were -0.81 (-4.0, 2.4), -0.08 (-3.1, 2.9), and ‑2.11 (‑5.3, 1.1) mcg/day for 200 mcg, 100 mcg, and 25 mcg dose groups, respectively. The mean AM plasma cortisol value did not show any consistent treatment effect with differences (and 95% confidence intervals) from placebo in the mean change from baseline to 12 weeks of 0.35 (‑1.4, 2.1), 0.12 (-1.5, 1.7), and -0.38 (-2.1, 1.3) mcg/dL for 200 mcg, 100 mcg, and 25 mcg dose groups, respectively. In this study, serum was assayed for ciclesonide and des‑ciclesonide [see Clinical Pharmacology (12.3)].

In a 6-week study in children 2 to 5 years of age with perennial allergic rhinitis, daily doses of 200 mcg, 100 mcg, and 25 mcg of OMNARIS Nasal Spray were compared to placebo nasal spray. Adrenal function was assessed by measurement of 24-hour urinary-free cortisol (in 15 to 22 patients per group) and morning plasma cortisol levels (in 28 to 30 patients per group) before and after 6 consecutive weeks of treatment. The ciclesonide-treated groups had a numerically greater decline in 24-hour urinary-free cortisol compared to the placebo-treated group. The differences (and 95% confidence intervals) from placebo in the mean change from baseline to 6 weeks were ‑2.04 (-4.4, 0.3), -1.96 (-4.5, 0.6), and ‑1.76 (‑4.3, 0.8) mcg/day for the 200 mcg, 100 mcg, and 25 mcg dose groups, respectively. The plasma cortisol also decreased numerically after treatment with ciclesonide. The differences (and 95% confidence intervals) from placebo in the mean change in plasma cortisol from baseline to 6 weeks were ‑1.04 (‑2.7, 0.7), -0.36 (-2.1, 1.4), and ‑0.12 (‑1.8, 1.6) mcg/dL for the 200 mcg, 100 mcg, and 25 mcg dose groups, respectively. In this study, serum was assayed for ciclesonide and des-ciclesonide [see Clinical Pharmacology (12.3)].

12.3 Pharmacokinetics

Absorption: Ciclesonide and des-ciclesonide have negligible oral bioavailability (both less than 1%) due to low gastrointestinal absorption and high first-pass metabolism. The intranasal administration of ciclesonide at recommended doses results in negligible serum concentrations of ciclesonide. However, the known active metabolite (des-ciclesonide) is detected in the serum of some patients after nasal inhalation of ciclesonide. The bioanalytical assay used has a lower limit of quantification of 25 pg/mL and 10 pg/mL, for ciclesonide and des-ciclesonide, respectively.

In healthy adults treated for two weeks with 50 to 800 mcg of ciclesonide nasal spray daily (n=6 in each treatment group), the peak serum concentrations of des-ciclesonide in all subjects were found to be below 30 pg/mL. Of those treated with 800 mcg and 400 mcg daily, 100% and 67% had detectable levels of des‑ciclesonide, respectively. With daily doses of 200 mcg or less, detectable serum levels of des-ciclesonide were not observed. The low systemic exposure following ciclesonide nasal spray administration was confirmed in a crossover study in twenty-nine healthy adults. The median Cmax was less than 10 pg/mL and 602 pg/mL following a single dose of ciclesonide nasal spray (300 mcg) and orally inhaled ciclesonide (320 mcg), respectively.

Distribution: Following intravenous administration of 800 mcg of ciclesonide, the volumes of distribution of ciclesonide and des-ciclesonide were approximately 2.9 L/kg and 12.1 L/kg, respectively. The percentage of ciclesonide and des-ciclesonide bound to human plasma proteins averaged ≥ 99% each, with ≤ 1% of unbound drug detected in the systemic circulation. Des‑ciclesonide is not significantly bound to human transcortin.

Metabolism: Ciclesonide is hydrolyzed to a biologically active metabolite, des-ciclesonide, by esterases. Des-ciclesonide undergoes further metabolism in the liver to additional metabolites mainly by the cytochrome P450 (CYP) 3A4 isozyme and to a lesser extent by CYP 2D6. The full range of potentially active metabolites of ciclesonide has not been characterized. After intravenous administration of ^14C-ciclesonide, 19.3% of the resulting radioactivity in the plasma is accounted for by ciclesonide or des-ciclesonide; the remainder may be a result of other, as yet, unidentified multiple metabolites.

Elimination: Following intravenous administration of 800 mcg of ciclesonide, the clearance values of ciclesonide and des-ciclesonide were high (approximately 152 L/h and 228 L/h, respectively). ^14C-labeled ciclesonide was predominantly excreted via the feces after intravenous administration (66%) indicating that excretion through bile is the major route of elimination. Approximately 20% or less of drug-related radioactivity was excreted in the urine.

Special Populations: The pharmacokinetics of intranasally administered ciclesonide have not been assessed in patient subpopulations because the resulting blood levels of ciclesonide and des-ciclesonide are insufficient for pharmacokinetic calculations. However, population pharmacokinetic analysis showed that characteristics of des-ciclesonide after oral inhalation of ciclesonide were not appreciably influenced by a variety of subject characteristics such as body weight, age, race, and gender.

Hepatic Impairment: Compared to healthy subjects, the systemic exposure (Cmax and AUC) in patients with liver impairment increased in the range of 1.4 to 2.7-fold after ex-actuator administration of 1280 mcg ciclesonide via oral inhalation. Dose adjustment in liver impairment is not necessary.

Renal Impairment: Studies in renally-impaired patients were not conducted since renal excretion of des-ciclesonide is a minor route of elimination (≤ 20%).

Pediatric: In pediatric subjects treated with 25 to 200 mcg of ciclesonide nasal spray daily, serum concentrations of des-ciclesonide were below 45 pg/mL, with the exception of one value of 64.5 pg/mL. In a 12-week study in children 6 to 11 years of age with perennial allergic rhinitis, des-ciclesonide was detected in 50% of the subjects treated with 200 mcg and in 5% of those treated with 100 mcg ciclesonide nasal spray daily. In a 6-week study in children 2 to 5 years of age with perennial allergic rhinitis, des-ciclesonide was detected in 41%, 22%, and 13% of the subjects treated with 200 mcg, 100 mcg, and 25 mcg ciclesonide nasal spray daily, respectively.

Drug-Drug Interactions: Based on in vitro studies in human liver microsomes, des-ciclesonide appears to have no inhibitory or induction potential on the metabolism of other drugs metabolized by cytochrome P450 enzymes. The inhibitory potential of ciclesonide on cytochrome P450 isoenzymes has not been studied. In vitro studies demonstrated that the plasma protein binding of des-ciclesonide was not affected by warfarin or salicylic acid, indicating no potential for protein binding-based drug interactions.

In a drug interaction study, co-administration of orally inhaled ciclesonide and oral ketoconazole, a strong inhibitor of cytochrome P450 3A4, increased the exposure (AUC) of the active metabolite of ciclesonide, des-ciclesonide, by approximately 3.6-fold at steady state, while levels of ciclesonide remained unchanged.

In another drug interaction study, co-administration of orally inhaled ciclesonide and oral erythromycin, a moderate inhibitor of cytochrome P450 3A4, had no effect on the pharmacokinetics of either des-ciclesonide or erythromycin.

13 NONCLINICAL TOXICOLOGY

13.1 Carcinogenesis, Mutagenesis, Impairment of Fertility

Two-year carcinogenicity studies in B6C3F1 mice and Wistar rats were conducted to assess the carcinogenic potential of ciclesonide. Ciclesonide demonstrated no tumorigenic potential in a study with mice that received oral doses up to 900 mcg/kg/day (approximately 20 and 10 times the MRHDID in adults and adolescents ≥ 12 years of age and children 6 to 11 years of age, respectively, on a mcg/m^2 basis) and a study with rats that received inhalation doses up to 193 mcg/kg/day (approximately 9 and 4 times the MRHDID in adults and adolescents ≥ 12 years of age and children 6 to 11 years of age, respectively, on a mcg/m^2 basis).

Ciclesonide was not mutagenic in an Ames test or in the Chinese hamster lung V79 cell/hypoxanthine-guanine phosphoribosyl transferase (HGPRT) forward mutation assay and was not clastogenic in a human lymphocyte chromosomal aberration assay or in an in vitro micronucleus test. However, ciclesonide was clastogenic in an in vivo mouse micronucleus test. The concurrent reference corticosteroid (dexamethasone) in this study showed similar findings.

Fertility and reproductive performance were unaffected in male and female rats dosed by the oral route up to 900 mcg/kg/day (approximately 45 times the MRHDID in adults based on mcg/m^2).

14 CLINICAL STUDIES

14.1 Seasonal and Perennial Allergic Rhinitis

Adults and Adolescent Patients 12 Years of Age and Older: The efficacy of OMNARIS Nasal Spray was evaluated in 3 randomized, double‑blind, parallel-group, multicenter, placebo-controlled clinical trials of 2 to 6 weeks duration conducted in the United States and Canada in adolescents and adults with allergic rhinitis. The three trials included a total of 1524 patients (495 males and 1029 females) of whom 79 were adolescents, ages 12 to 17 years. The racial distribution in these three trials included 1374 Caucasians, 69 Blacks, 31 Asians, and 50 patients classified as Other. Of the 1524 patients, 546 patients received OMNARIS Nasal Spray 200 mcg once daily administered as 2 sprays in each nostril. Patients enrolled in the studies were 12 to 86 years of age with a history of seasonal or perennial allergic rhinitis, a positive skin test to at least one relevant allergen, and active symptoms of allergic rhinitis at study entry. Assessment of efficacy in these trials was based on patient recording of four nasal symptoms (runny nose, nasal itching, sneezing, and nasal congestion) on a 0-3 categorical severity scale (0=absent, 1=mild, 2=moderate, and 3=severe) as reflective or instantaneous scores. Reflective scoring required the patients to record symptom severity over the previous 12 hours; the instantaneous scoring required patients to record symptom severity at the time of recording. The results of these trials showed that patients treated with OMNARIS Nasal Spray 200 mcg once daily exhibited statistically significantly greater decreases in total nasal symptom scores than placebo-treated patients. Secondary measures of efficacy were also generally supportive.

Dose-Ranging Trial: One of the three trials was a 2-week dose-ranging trial that evaluated efficacy of four doses of OMNARIS Nasal Spray in patients with seasonal allergic rhinitis. The primary efficacy endpoint was the difference from placebo in the change from baseline of the sum of morning and evening reflective total nasal symptom score averaged over the 2-week treatment period. Results of the primary efficacy endpoint are shown in Table 3. In this trial OMNARIS Nasal Spray 200 mcg once daily was statistically significantly different from placebo, but the lower doses were not statistically significantly different from placebo.

Table 3 Mean change in reflective total nasal symptom score over 2 weeks in patients with seasonal allergic rhinitis
Treatment | N | Baseline* | Change from Baseline | Difference from Placebo**
Treatment | N | Baseline* | Change from Baseline | Estimate | 95% CI | p-value
Seasonal Allergic Rhinitis Trial – Reflective total nasal symptom score
Ciclesonide 200 mcg | 144 | 18.8 | -5.73 | -1.35 | (-2.43, -0.28) | 0.014
Ciclesonide 100 mcg | 145 | 18.7 | -5.26 | -0.88 | (-1.96, 0.19) | 0.11
Ciclesonide 50 mcg | 143 | 18.4 | -4.82 | -0.44 | (-1.52, 0.63) | 0.42
Ciclesonide 25 mcg | 146 | 18.7 | -4.74 | -0.35 | (-1.42, 0.71) | 0.51
Placebo | 148 | 17.8 | -4.38
* Sum of AM and PM Scores; Maximum score = 24
** Estimates, 95% Confidence Intervals, and p-values were obtained from repeated measures ANCOVA analysis with treatment, baseline, day, and treatment by day interaction effects included in the model.

Seasonal Allergic Rhinitis Trial: The second trial was a 4-week single dose level trial conducted in patients with seasonal allergic rhinitis. The primary efficacy endpoint in the seasonal allergic rhinitis trial was the difference from placebo in the change from baseline of the average of morning and evening reflective total nasal symptom score averaged over the first 2 weeks of treatment. In this trial, OMNARIS Nasal Spray 200 mcg once daily was statistically significantly different from placebo (Table 4). Statistically significant differences in the morning pre-dose instantaneous total nasal symptom score indicate that the effect was maintained over the full 24-hour dosing interval.

Perennial Allergic Rhinitis Trial: The third trial was a 6-week single dose level trial conducted in patients with perennial allergic rhinitis. The primary efficacy endpoint in the perennial allergic rhinitis trial was the difference from placebo in the change from baseline of the average of morning and evening reflective total nasal symptom score averaged over the 6 weeks of treatment. In this trial, OMNARIS Nasal Spray 200 mcg once daily was statistically significantly different from placebo (Table 4). Statistically significant differences in the morning pre-dose instantaneous total nasal symptom score indicate that the effect was maintained over the full 24-hour dosing interval.

Table 4 Mean changes in reflective total nasal symptom score and instantaneous total nasal symptom score in allergic rhinitis trials
Treatment | N | Baseline* | Change from Baseline | Difference from Placebo**
Treatment | N | Baseline* | Change from Baseline | Estimate | 95% CI | p-value
Seasonal Allergic Rhinitis Trial – Reflective total nasal symptom score
Ciclesonide 200 mcg | 162 | 8.96 | -2.40 | -0.90 | (-1.36, -0.45) | <0.001
Placebo | 162 | 8.83 | -1.50
Seasonal Allergic Rhinitis Trial – Instantaneous total nasal symptom score
Ciclesonide 200 mcg | 162 | 8.45 | -1.87 | -0.84 | (-1.30, -0.39) | <0.001
Placebo | 162 | 8.33 | -1.03
Perennial Allergic Rhinitis Trial – Reflective total nasal symptom score
Ciclesonide 200 mcg | 232 | 7.59 | -2.51 | -0.62 | (-0.97, -0.28) | <0.001
Placebo | 229 | 7.72 | -1.89
Perennial Allergic Rhinitis Trial – Instantaneous total nasal symptom score
Ciclesonide 200 mcg | 232 | 7.05 | -1.99 | -0.53 | (-0.90, -0.17) | 0.004
Placebo | 229 | 7.05 | -1.46
* Mean of AM and PM score from reflective total nasal symptom score; Mean of AM score for instantaneous total nasal symptom score; Maximum = 12
** Estimates, 95% Confidence Intervals, and p-values were obtained from repeated measures ANCOVA analysis with treatment, baseline, day, and treatment by day interaction effects included in the model.

Onset of action: Onset of action was evaluated in two environmental exposure unit studies in patients with seasonal allergic rhinitis receiving a single dose of OMNARIS Nasal Spray 200 mcg. Results from these two studies did not demonstrate a replicate onset of action within the assessment period. Onset of action was also evaluated in the 4-week seasonal allergic rhinitis and in the 6-week perennial allergic rhinitis trial by frequent recording of instantaneous symptom score after the first dose. In these trials, onset of effect was seen within 24 to 48 hours with further symptomatic improvement observed over 1 to 2 weeks in seasonal allergic rhinitis and 5 weeks in perennial allergic rhinitis.

Pediatric Patients Aged 6 to 11 Years: The efficacy of OMNARIS Nasal Spray was evaluated in two randomized, double-blind, parallel-group, multicenter, placebo-controlled clinical trials in 1282 patients 6 to 11 years of age with allergic rhinitis. Of the two trials, one was 2 weeks in duration conducted in patients with seasonal allergic rhinitis that evaluated efficacy of 200 mcg and 100 mcg of OMNARIS Nasal Spray once daily. The other trial was 12 weeks in duration conducted in patients with perennial allergic rhinitis that evaluated efficacy of 200 mcg, 100 mcg, and 25 mcg of OMNARIS Nasal Spray once daily. Of the total number of patients enrolled in the 2 studies, 380 were treated with 200 mcg of OMNARIS Nasal Spray once daily. The primary efficacy endpoint was the difference from placebo in the change from baseline of the average of morning and evening reflective total nasal symptom score averaged over 2 weeks of treatment in the seasonal allergic rhinitis trial and over the first 6 weeks of treatment in the perennial allergic rhinitis trial. In the 2-week trial in patients with seasonal allergic rhinitis, the OMNARIS Nasal Spray 200 mcg once daily dose was statistically significantly different from placebo, but the 100 mcg once daily dose was not statistically significantly different from placebo. The efficacy results for the seasonal allergic rhinitis trial are shown in Table 5.

Table 5 Mean changes in reflective total nasal symptom score in 1 seasonal allergic rhinitis trial in children 6 to 11 years of age
Treatment | N | Baseline* | Change from Baseline | Difference from Placebo**
Treatment | N | Baseline* | Change from Baseline | Estimate | 95% CI | p-value
Reflective total nasal symptom score
Ciclesonide 200 mcg | 215 | 8.25 | -2.46 | -0.39 | (-0.76, -0.02) | 0.040
Ciclesonide 100 mcg | 199 | 8.41 | -2.38 | -0.32 | (-0.69, 0.06) | 0.103
Placebo | 204 | 8.41 | -2.07
* Mean of AM and PM score from reflective total nasal symptom score; Maximum = 12
** Estimates, 95% Confidence Intervals, and p-values were obtained from repeated measures ANCOVA analysis with treatment, baseline, day, and treatment by day interaction effects included in the model.

In the 12-week trial in patients with perennial allergic rhinitis, none of the ciclesonide doses were statistically significantly different from placebo. The means and 95% confidence intervals for the differences (OMNARIS Nasal Spray minus placebo) between OMNARIS Nasal Spray 200 mcg, 100 mcg, and 25 mcg treatment groups and placebo were ‑0.31 (-0.75, 0.13), 0.02 (-0.41, 0.46), and 0.09 (-0.35, 0.53), respectively.

Pediatric Patients Aged 2 to 5 Years: Efficacy of OMNARIS Nasal Spray in patients 2 to 5 years of age has not been established [see Pediatric Use (8.4)].

16 HOW SUPPLIED/STORAGE AND HANDLING

OMNARIS is supplied in an amber glass bottle and provides for nasal delivery with a manual metered pump. OMNARIS Nasal Spray is supplied with an oxygen absorber sachet and enclosed in a foil pouch. The contents of one 12.5 gram bottle provide 120 actuations, after initial priming. Each spray delivers 50 mcg of ciclesonide from the nasal actuator. Prior to initial use, OMNARIS Nasal Spray must be gently shaken and then the pump must be primed by actuating eight times. The OMNARIS Nasal Spray bottle has been filled with an excess to accommodate the priming activity. The bottle should be discarded after removal from the foil pouch either after 120 sprays following initial priming (since the amount of ciclesonide delivered per spray thereafter may be substantially less than the labeled dose) or after 4 months. Patient instructions are also provided.

Store at 25°C (77°F); excursions permitted to 15-30°C (59-86°F) [See USP Controlled Room Temperature]. Do not freeze. Shake gently before use. Keep out of reach of children.

Omnaris Nasal Spray 50 mcg, 120 metered sprays; net fill weight 12.5 g.
NDC 70515-701-01

17 PATIENT COUNSELING INFORMATION

See FDA-approved patient labeling (Patient Information and Instructions for Use).

17.1 Local Nasal Effects

Patients should be informed that treatment with OMNARIS Nasal Spray may lead to adverse reactions, which include epistaxis and nasal ulceration. Candida infection may also occur with treatment with OMNARIS Nasal Spray. In addition, nasal corticosteroids are associated with nasal septal perforation and impaired wound healing. Avoid spraying OMNARIS Nasal Spray directly onto the nasal septum. Patients who have experienced recent nasal ulcers, nasal surgery, or nasal trauma should not use OMNARIS Nasal Spray until healing has occurred [see Warnings and Precautions (5.1)].

17.2 Cataracts and Glaucoma

Patients should be informed that glaucoma and cataracts are associated with nasal and inhaled corticosteroid use. The patient should inform his/her health care provider if a change in vision is noted while using OMNARIS Nasal Spray [see Warnings and Precautions (5.2)].

17.3 Immunosuppression

Patients who are on immunosuppressive doses of corticosteroids should be warned to avoid exposure to chickenpox or measles, and if exposed, to consult their physician without delay. Patients should be informed of potential worsening of existing tuberculosis, fungal, bacterial, viral or parasitic infections, or ocular herpes simplex [see Warnings and Precautions (5.3)].

17.4 Use Daily

Patients should use OMNARIS Nasal Spray at regular intervals since its effectiveness depends on its regular use. In clinical trials, the onset of effect was seen within 24 to 48 hours with further symptomatic improvement observed over 1 to 2 weeks in seasonal allergic rhinitis and 5 weeks in perennial allergic rhinitis. Initial assessment of response should be made during this time frame and periodically until the patient’s symptoms are stabilized. The patient should take the medication as directed and should not exceed the prescribed dosage. The patient should contact the physician if symptoms do not improve by a reasonable time or if the condition worsens.

17.5 Keep Spray Out of Eyes

Patients should be informed to avoid spraying OMNARIS Nasal Spray in their eyes.

17.6 Storage and Handling

It is important that the bottle is gently shaken prior to use to ensure that a consistent amount is dispensed per actuation. The bottle should be discarded after 120 actuations following initial priming or after 4 months after the bottle is removed from the foil pouch, whichever occurs first.

Manufactured for
Covis Pharma
Zug, 6300 Switzerland
Made in Germany
© 2018 Covis Pharma and AstraZeneca group of companies. All rights reserved

OMNARIS is a registered trademark of AstraZeneca group of companies and is used under license.

May 2019

Patient Information

OMNARIS® [Ŏm-nĕ’-rĭs] (ciclesonide) Nasal Spray, 50 mcg

Important Note: For Intranasal Use Only. Avoid spraying in eyes or directly onto the nasal septum (the wall between the two nostrils).

Read this leaflet before you start using OMNARIS Nasal Spray and each time you refill your prescription. This leaflet does not take the place of talking with your healthcare provider about your medical condition or your treatment. If you have any questions about OMNARIS Nasal Spray, ask your healthcare provider or pharmacist.

What is OMNARIS Nasal Spray?

OMNARIS Nasal Spray contains a medicine called ciclesonide, which is a synthetic corticosteroid (a substance that reduces inflammation). This medicine is used to treat nasal symptoms (i.e., runny nose, itchy nose, sneezing, and nasal congestion) that happen with:

- Seasonal nasal allergy in adults and children 6 years of age and older.
- Year-round nasal allergy symptoms in adults and adolescents 12 years of age and older.

How do I use OMNARIS Nasal Spray?

Use your nasal spray exactly as prescribed by your healthcare provider.

Seasonal allergy symptoms may improve over 1 to 2 weeks; year-round allergy symptoms may improve over 5 weeks. If your symptoms do not improve or get worse, call your healthcare provider.

Dosage

- OMNARIS Nasal Spray is used 1 time each day, 2 sprays in each nostril.
- Do not use more than a total of 2 sprays in each nostril each day.

Before using OMNARIS Nasal Spray, tell your healthcare provider about all of your medical conditions, including if you:

- have or have had nasal sores, nasal surgery, or nasal injury. Do not use OMNARIS Nasal Spray until your nose has healed.
- have eye problems, including glaucoma and cataracts. You should have regular eye exams.
- have an immune system problem.
- have any type of viral, bacterial, or fungal infection.
- are exposed to chickenpox or measles.
- are pregnant or plan to become pregnant. It is not known if OMNARIS Nasal Spray may harm your unborn baby.
- are breastfeeding or plan to breastfeed. It is not known if the medicine in OMNARIS Nasal Spray passes into your breast milk and if it can harm your baby.

Tell your healthcare provider about all the medicines you take, including prescription and over-the-counter medicines, vitamins, and herbal supplements.

OMNARIS Nasal Spray and other medicines may interact with each other. This may cause serious side effects. Especially tell your healthcare provider if you take antifungal or anti-HIV medicines.

Know the medicines you take. Keep a list of them to show your healthcare provider and pharmacist when you get a new medicine.

What are the possible side effects of OMNARIS Nasal Spray?

OMNARIS Nasal Spray may cause serious side effects, including:

- Nasal Problems. Symptoms of nasal problems may include:
  - Nose bleeds.
  - Crusting in the nose.
  - Sores (ulcers) in the nose.
  - Hole in the cartilage of the nose (nasal septal perforation). A whistling sound when you breathe may be a symptom of nasal septum perforation.
  - Thrush (candida), a fungal infection in your nose and throat. Tell your healthcare provider if you have any redness or white colored patches in your nose or mouth.
  - Slow wound healing. You should not use OMNARIS Nasal Spray until your nose has healed if you have a sore in your nose, have had surgery on your nose, or if your nose has been injured.
- Eye problems, including glaucoma and cataracts. You should have regular eye exams while you use OMNARIS Nasal Spray.
- Serious allergic reactions. Call your healthcare provider or get emergency medical care if you get any of the following signs of a serious allergic reaction:
  - rash
  - hives
  - swelling of your face, mouth, and tongue
  - breathing problems
  - low blood pressure
- Weakened immune system and increased chance of getting infections (immunosuppression). Taking medicines that weaken your immune system makes you more likely to get infections and can make certain infections worse. These infections may include tuberculosis (TB), herpes simplex infections of the eyes (ocular herpes simplex infections), and infections caused by fungi, bacteria, viruses, and parasites. You should avoid contact with people who have a contagious disease such as chickenpox or measles while using OMNARIS Nasal Spray. If you come in contact with someone who has chickenpox or measles, call your healthcare provider right away. Symptoms of an infection may include:
  - fever
  - pain
  - aches
  - chills
  - feeling tired
  - nausea
  - vomiting
- Reduced adrenal function (adrenal insufficiency). Adrenal insufficiency happens when your adrenal glands do not make enough steroid hormones. This can happen when you stop taking oral corticosteroid medicines (such as prednisone) and start taking medicine containing a steroid inhaled into the lungs or for use in the nose. Symptoms of adrenal insufficiency may include:
  - Tiredness
  - Weakness
  - Nausea and vomiting
  - Low blood pressure
- Slowed growth in children. A child taking OMNARIS Nasal Spray should have their growth checked regularly.

The most common side effects of OMNARIS Nasal Spray include:

- headache
- nose bleeds
- stuffy nose
- ear pain
- sore throat
- dizziness

These are not all the possible side effects of OMNARIS Nasal Spray. Tell your healthcare provider about any side effects that bother you or do not go away.

Call your healthcare provider for medical advice about side effects. You may report side effects to FDA at 1-800-FDA-1088.

What are the ingredients in OMNARIS Nasal Spray?

Active ingredient: ciclesonide

Inactive ingredients: purified water, microcrystalline cellulose, carboxymethylcellulose sodium, hypromellose, potassium sorbate and edetate sodium; and hydrochloric acid to adjust the pH to 4.5.

This leaflet does not contain all of the information about your medicine. If you have any questions, ask your healthcare provider or pharmacist.

You may want to read this leaflet again. Please DO NOT THROW IT AWAY until you have finished your medicine.

Patient’s Instructions for Use

OMNARIS Nasal Spray is supplied in an amber glass bottle in a protective plastic sleeve and should be handled with care.

Preparing for Use

1. Remove OMNARIS Nasal Spray from its foil pouch. Count 4 months from today and write this new date on the sticker on the carton (the date that is 4 months after removing the bottle from the foil pouch). Peel off the sticker and place it in the space on your nasal spray bottle. It is important that you throw away the nasal spray bottle after this date.
2. Priming OMNARIS Nasal Spray. Before you use OMNARIS Nasal Spray for the first time, you will need to prime the bottle. Hold the bottle upright and shake the bottle gently. To prime OMNARIS Nasal Spray, fully press down on the finger rests of the applicator eight times (See Figure 1 and Figure 2). If you do not use the nasal spray for 4 days, you will need to shake the bottle gently, and prime the pump again by spraying one time, or until you see a fine mist.

Figure 1

Using the Spray

1. Blow your nose to clear your nostrils, if needed.
2. Shake the bottle gently and remove the dust cap (See Figure 1).
3. Hold the bottle firmly with your index and middle finger on either side of the applicator (on finger rests) while supporting the base of the bottle with your thumb (See Figure 2).

Figure 2

4. Insert applicator tip into one nostril, and close the other nostril with your finger (See Figure 3).

Figure 3

5. Tilt your head forward slightly. Keep the bottle upright, and press the finger rests quickly and firmly to activate the pump. Breathe in (inhale) through your nose as you spray (See Figure 4). Try not to get any spray in your eyes or directly on your nasal septum (the wall between the two nostrils).

Figure 4

6. Repeat steps 3-5 for the second spray in the same nostril and for each spray in the other nostril.

How do I store OMNARIS Nasal Spray?

  a. Keep OMNARIS Nasal Spray clean and dry at all times.
  b. Store OMNARIS Nasal Spray between 59°F and 86°F.
  c. Do not freeze.
  d. Keep OMNARIS Nasal Spray and all medicines out of the reach of children.

How do I know when the OMNARIS Nasal Spray bottle is empty?

Each bottle of OMNARIS Nasal Spray contains enough medicine for you to spray medicine from the bottle 120 times. Do not use a bottle of OMNARIS Nasal Spray after 120 sprays (not counting the priming sprays) have been used or after the “discard by date” you wrote on the sticker when you opened the foil pouch. You may still see some medicine in the bottle. Talk with your healthcare provider before your supply of OMNARIS Nasal Spray runs out to see if you should get a refill of your medicine.

Applicator Cleaning Instructions

Wipe the applicator tip with a clean tissue and replace the dust cap, after you use your nasal spray each day (See Figure 5).

Figure 5

If the applicator is clogged or needs more thorough cleaning, use the following cleaning instructions; (Do not try to unblock the tiny spray hole on the applicator with a pin or other sharp object. Do not twist or try to remove the white plastic pump attached to the medicine bottle.)

1. Remove the dust cap, hold the white plastic pump firmly with one hand and then carefully pull upwards to free the applicator (See Figure 6).

Figure 6

2. Wash the dust cap and applicator with warm water (See Figure 7).

Figure 7

3. Dry the applicator, and put it back on the bottle. The applicator will snap into place when properly positioned (See Figure 8).

Figure 8

4. Prime the unit with one spray or until you see a fine mist.
5. Put the dust cap back on the applicator.

Manufactured for
Covis Pharma.
Zug, 6300 Switzerland
Made in Germany
© 2018 Covis Pharma and AstraZeneca group of companies. All rights reserved.

OMNARIS is a registered trademark of AstraZeneca group of companies and is used under license.

Revised: June 2018

PRINCIPAL DISPLAY PANEL - 50 mcg Carton Label

50 mcg Carton Label

NDC 70515-701-01

Net Contents: 12.5 g

omnaris®
(ciclesonide) Nasal Spray, 50 mcg

120 Metered Actuations

FOR INTRANASAL USE ONLY

Rx Only

FRAGILE: Glass bottle inside.

Attention Pharmacist:
Dispense with accompanying Patient’s Instructions for Use.

Attention Patient:
See Patient’s Instructions for Use and cleaning
instructions before using this product.

Discard OMNARIS® 4 months after opening foil pouch.

COVIS

GTIN: 00370515701014

LOT: XXXXXX

EXP: MM-YYYY

SERIAL NO:XXXXXXXXXXXXXX

Discard OMNARIS®
4 months after opening
foil pouch.

Discard After Date:

___/___/___

Peel off and
place directly on
nasal spray bottle.

Manufactured for
Covis Pharma
Zug, 6300 Switzerland
Made in Germany

© 2019 Covis Pharma
All rights reserved.

Contents: A manual
metered pump spray
unit containing a
hypotonic aqueous
suspension of ciclesonide;
microcrystalline cellulose,
carboxymethylcellulose
sodium, hypromellose,
potassium sorbate,
edetate sodium adjusted
to a target pH of 4.5 with
hydrochloric acid.

Usual Dosage: See
package insert.

Avoid spraying in eyes.

Keep out of reach of
children.

Shake gently before use.

Store at 25°C (77°F);
excursions permitted
to 15°–30°C (59°–86°F)
[see USP Controlled
Room Temperature].
Do not freeze.